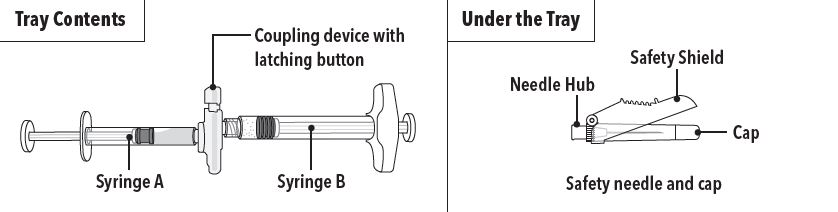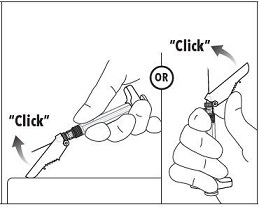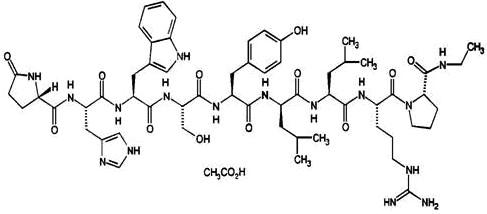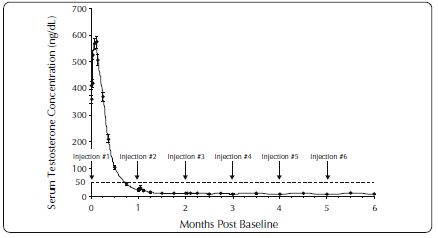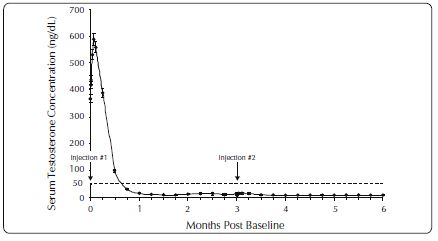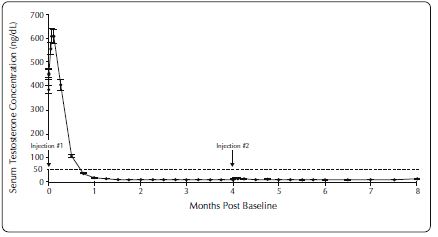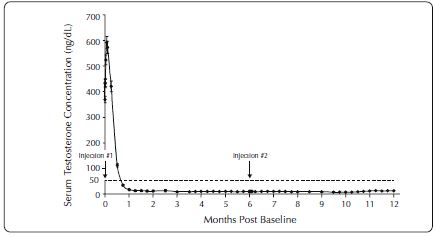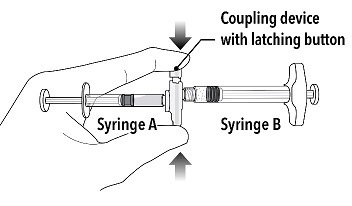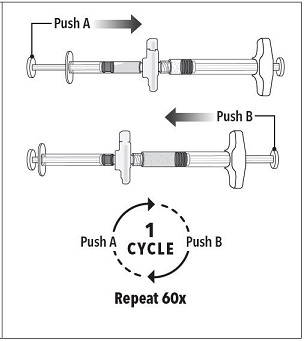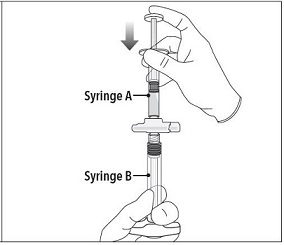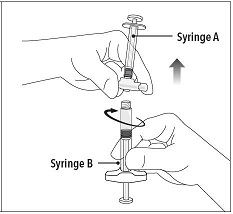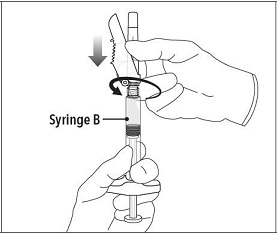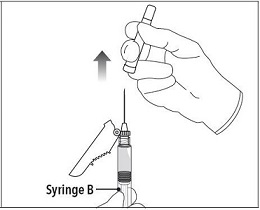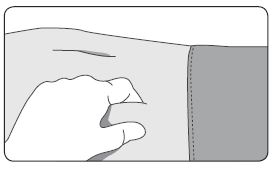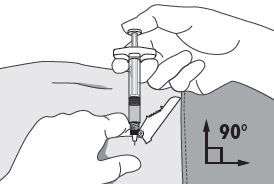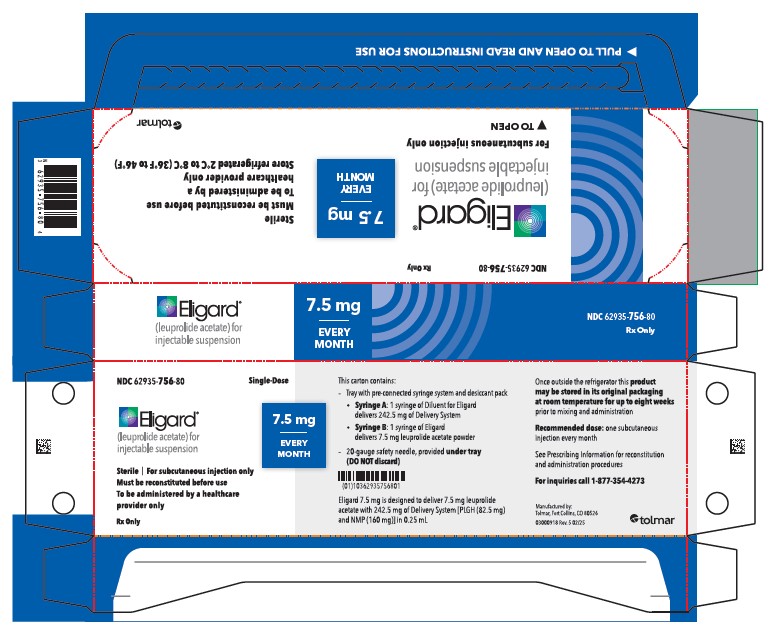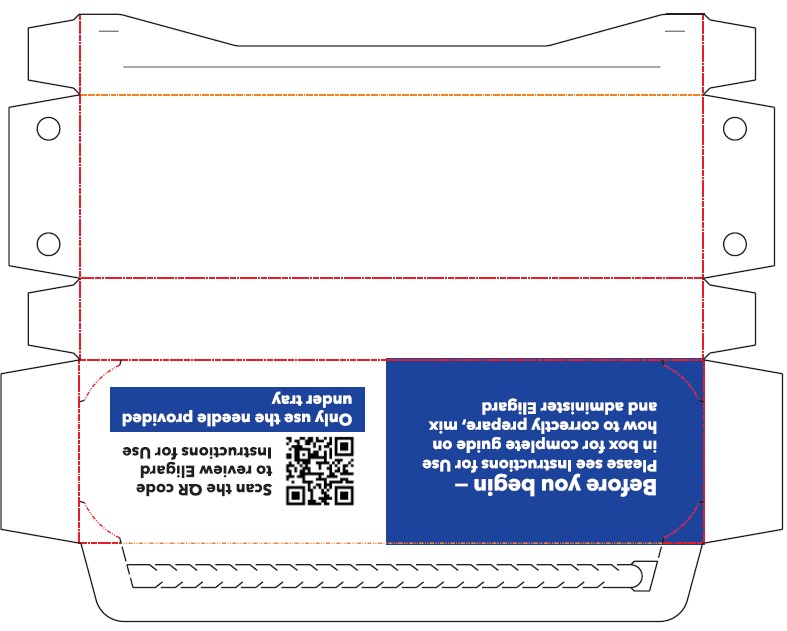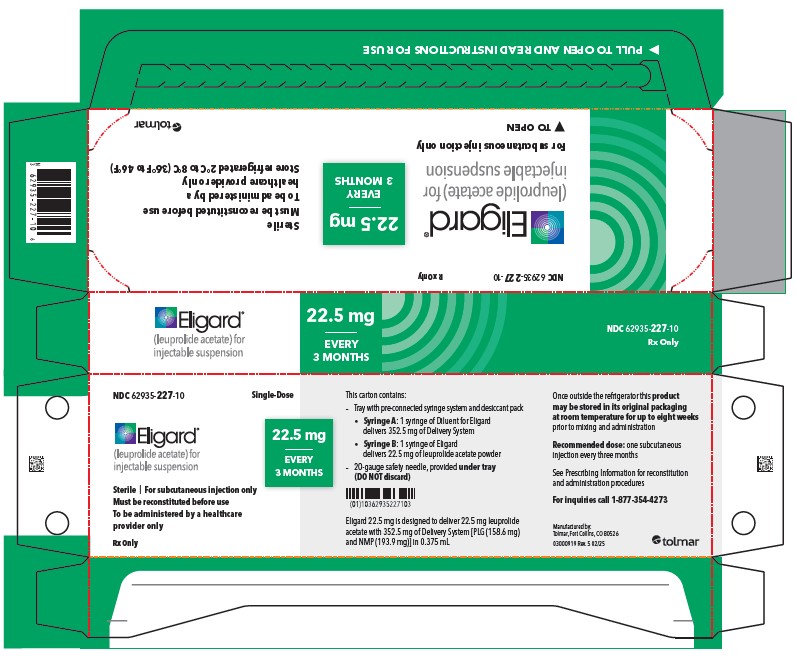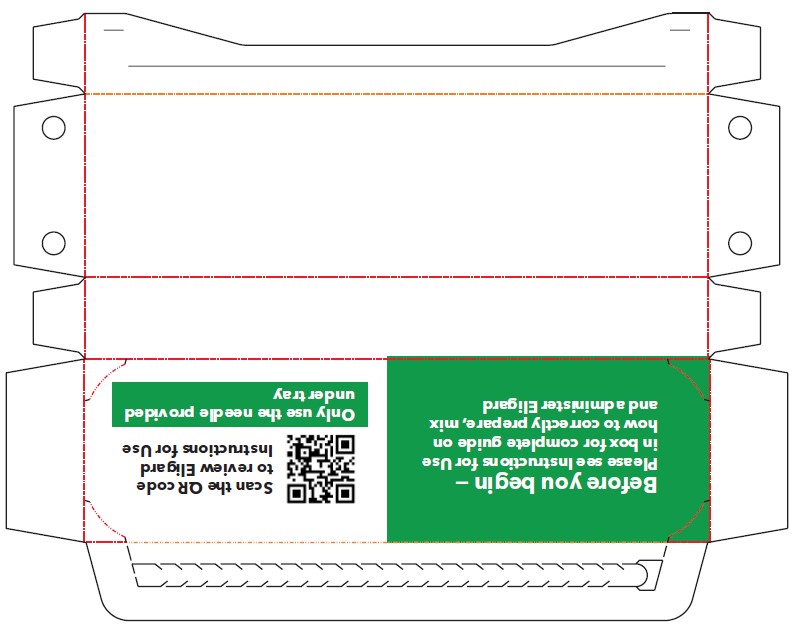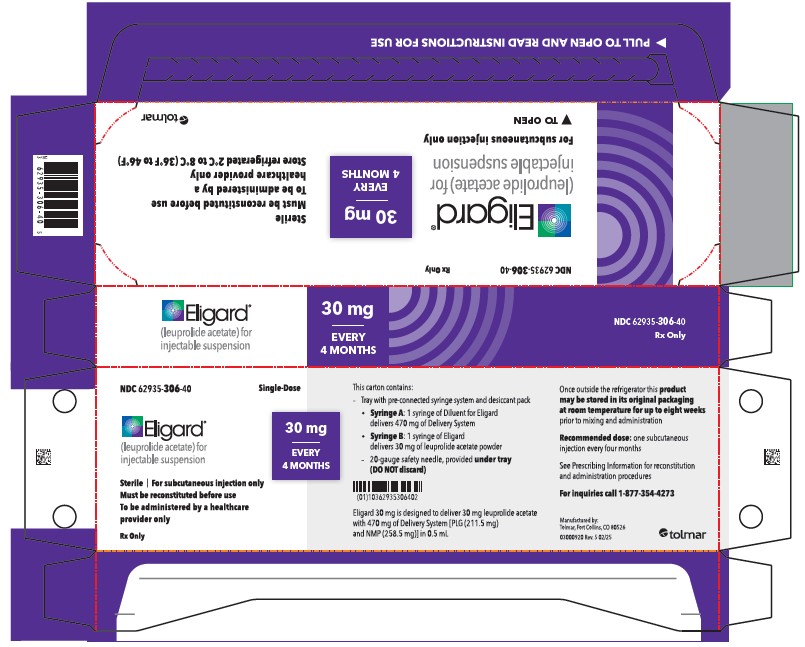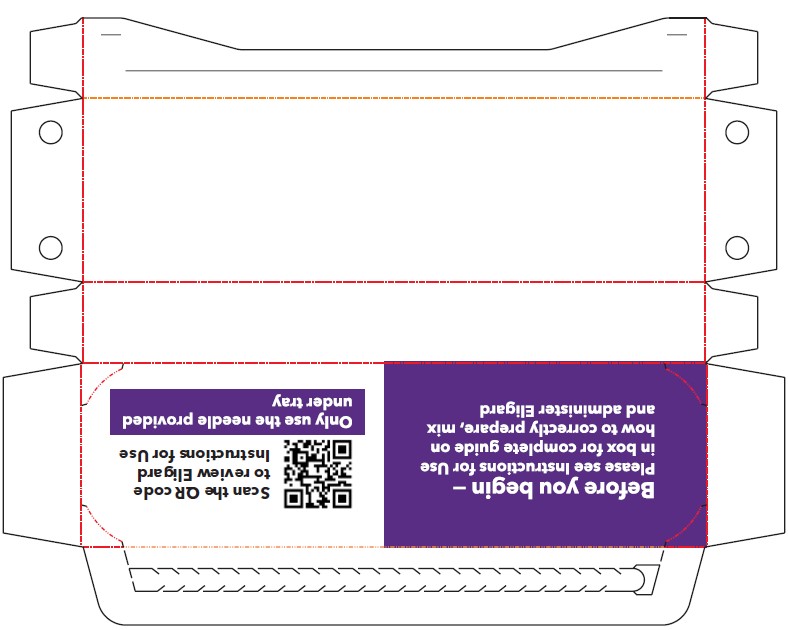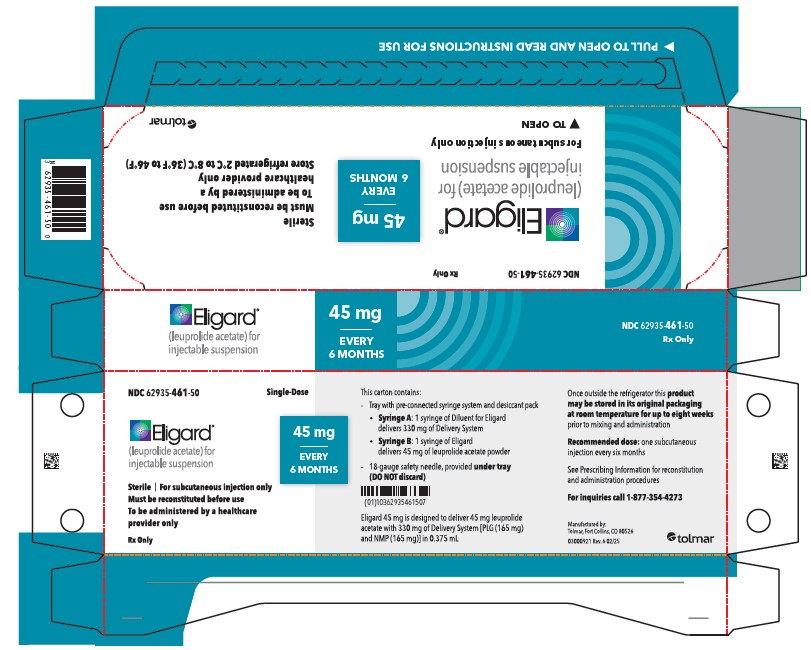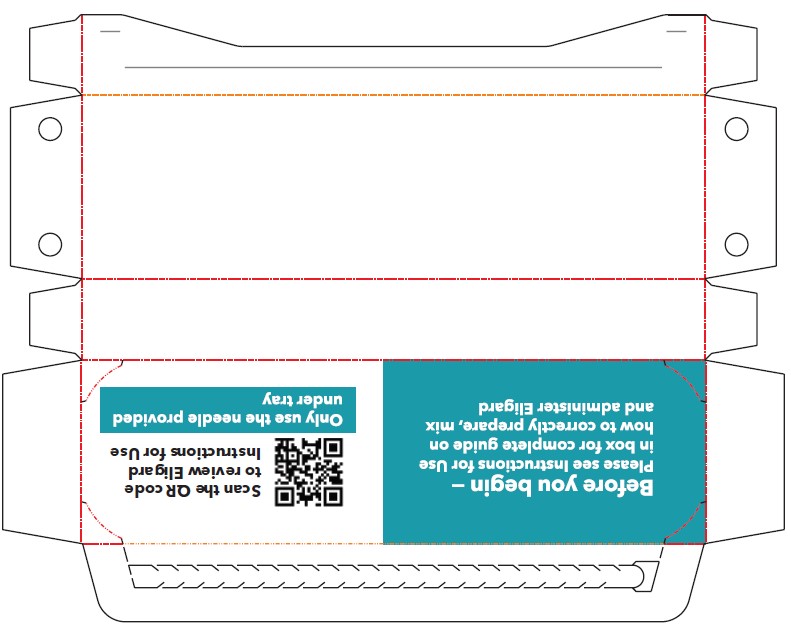 DRUG LABEL: Eligard
NDC: 62935-756 | Form: INJECTION, SUSPENSION, EXTENDED RELEASE
Manufacturer: TOLMAR Inc.
Category: prescription | Type: HUMAN PRESCRIPTION DRUG LABEL
Date: 20250224

ACTIVE INGREDIENTS: LEUPROLIDE ACETATE 7.5 mg/0.25 mL
INACTIVE INGREDIENTS: METHYL PYRROLIDONE 160 mg/0.25 mL; POLY(DL-LACTIC-CO-GLYCOLIC ACID), (50:50; 46000 MW) 82.5 mg/0.25 mL

HIGHLIGHTS OF PRESCRIBING INFORMATION

These highlights do not include all the information needed to use ELIGARD® safely and effectively. See full prescribing information for ELIGARD.
ELIGARD (leuprolide acetate) for injectable suspension, for subcutaneous use
Initial U.S. Approval: 2002

RECENT MAJOR CHANGES

Warnings and Precautions (5.6) 02/2025
Dosage and Administration (2) 02/2025

1 INDICATIONS AND USAGE

ELIGARD is a gonadotropin releasing hormone (GnRH) agonist indicated for the treatment of advanced prostate cancer. (1)

2 DOSAGE AND ADMINISTRATION

ELIGARD is administered subcutaneously based on the following recommended dose and schedule:

- 7.5 mg subcutaneously every month (2.1)
- 22.5 mg subcutaneously every 3 months (2.1)
- 30 mg subcutaneously every 4 months (2.1)
- 45 mg subcutaneously every 6 months (2.1)

See Full Prescribing Information for preparation and administration instructions. (2.2, 2.3)

3 DOSAGE FORMS AND STRENGTHS

- Injectable suspension: 7.5 mg (3)
- Injectable suspension: 22.5 mg (3)
- Injectable suspension: 30 mg (3)
- Injectable suspension: 45 mg (3)

4 CONTRAINDICATIONS

- Known hypersensitivity to GnRH, GnRH agonist analogs or any of the components of ELIGARD (4)

5 WARNINGS AND PRECAUTIONS

- Tumor Flare: Transient increase in serum levels of testosterone during treatment may result in worsening of symptoms or onset of new signs and symptoms during the first few weeks of treatment, including bone pain, neuropathy, hematuria, bladder outlet obstruction, ureteral obstruction, or spinal cord compression. Monitor patients at risk closely and manage as appropriate. (5.1, 5.7)
- Hyperglycemia and diabetes: Hyperglycemia and an increased risk of developing diabetes have been reported in men receiving GnRH analogs. Monitor blood glucose level and manage according to current clinical practice. (5.2)
- Cardiovascular diseases: Increased risk of myocardial infarction, sudden cardiac death and stroke has been reported in men. Monitor for cardiovascular disease and manage according to current clinical practice. (5.3)
- Effect on QT/QTc Interval: Androgen deprivation therapy may prolong the QT interval. Consider risks and benefits. (5.4)
- Convulsions have been observed in patients with or without a history of predisposing factors. Manage convulsions according to the current clinical practice. (5.5)
- Severe Cutaneous Adverse Reactions (SCARs), including Stevens-Johnson syndrome/toxic epidermal necrolysis, occurred in patients treated with ELIGARD. Interrupt ELIGARD if signs or symptoms of SCARs develop. Permanently discontinue if SCARs are confirmed. (5.6)
- Embryo-Fetal Toxicity: May cause fetal harm. (5.8, 8.1)

6 ADVERSE REACTIONS

- Most common adverse reactions in clinical studies (incidence ≥ 5%): Malaise, fatigue, hot flashes/sweats, and testicular atrophy. (6.1)
- As with other GnRH agonists, other adverse reactions, including decreased bone density and rare cases of pituitary apoplexy have been reported. (6.1, 6.2)

To report SUSPECTED ADVERSE REACTIONS, contact Tolmar at 1-888-354-4273 or FDA at 1-800-FDA-1088 or www.fda.gov/medwatch.

8 USE IN SPECIFIC POPULATIONS

- Females and males of reproductive potential: ELIGARD may impair fertility. (8.3)
- Pediatric: Safety and effectiveness in pediatric patients have not been established. (8.4)
- Geriatric: This label reflects clinical trials for ELIGARD in prostate cancer where the majority of subjects were at least 65 years of age (8.5).

FULL PRESCRIBING INFORMATION

1 INDICATIONS AND USAGE

ELIGARD is indicated for the treatment of advanced prostate cancer.

2 DOSAGE AND ADMINISTRATION

2.1 Recommended Dosage

ELIGARD is administered subcutaneously and provides continuous release of leuprolide acetate over a one-, three-, four-, or six-month treatment period (Table 1). ELIGARD must be administered by a healthcare provider. The injection delivers the dose of leuprolide acetate incorporated in a polymer formulation.

Table 1. ELIGARD Recommended Dosing

Dosage | 7.5 mg | 22.5 mg | 30 mg | 45 mg
Recommended dose | 1 injection every month | 1 injection every 3 months | 1 injection every 4 months | 1 injection every 6 months

As with other drugs administered by subcutaneous injection, the injection site should vary periodically. The specific injection location should be an area with sufficient soft or loose subcutaneous tissue. In clinical trials, the injections were administered in the upper- or mid-abdominal area. Avoid areas with brawny or fibrous subcutaneous tissue or locations that could be rubbed or compressed (i.e., with a belt or clothing waistband).

In patients treated with GnRH analogues for prostate cancer, treatment is usually continued upon development of metastatic castration-resistant prostate cancer.

2.2 Preparation Instructions

Use aseptic technique throughout the procedure. As with other similar agents, the use of gloves is recommended during mixing and administration. Allow the product to reach room temperature before mixing. Once mixed, the product must be administered within 30 minutes or it should be discarded.

ELIGARD is packaged in a carton containing:

- Tray containing pre-connected syringe system and desiccant pack
- Prescribing information
- Sterile safety needle and cap (located under the tray in carton)

Follow the detailed instructions below to ensure correct preparation of ELIGARD prior to administration:

Step 1

On a clean field open the tray by tearing off the foil from the corner and remove the contents. Discard the desiccant pack. Remove the pre-connected syringe system from the tray. Open the sterile safety needle package by peeling back the paper tab. Note: Syringe A and Syringe B should not be lined-up yet. The product should only be administered with the co-packaged, sterile safety needle.

Step 2

Grasp the latching button on the coupling device with your finger and thumb and press until you hear a snapping sound. The two syringes will be aligned.

Do not bend the pre-connected syringe system.

Step 3

Holding the syringes in a horizontal position, transfer the liquid contents of Syringe A into the leuprolide acetate powder contained in Syringe B. Thoroughly mix the product for 60 cycles by pushing the contents back and forth between both syringes to obtain a uniform suspension.

- A cycle is one push of the Syringe A plunger and one push of the Syringe B plunger.
- When thoroughly mixed, the suspension will appear light tan to tan (ELIGARD 7.5 mg) or colorless to pale yellow (ELIGARD 22.5 mg, 30 mg, and 45 mg).

Note: Product must be mixed as described; shaking will NOT provide adequate mixing. Do not bend.

Step 4

After mixing, hold the syringes vertically (upright) with Syringe B (wide syringe) on the bottom. The syringes should remain securely coupled. Transfer all of the mixed product into Syringe B by depressing the Syringe A plunger and slightly withdrawing the Syringe B plunger.

Step 5

While ensuring the Syringe A plunger is fully pushed down, hold the coupling device and unscrew Syringe B. This will disconnect Syringe B from the coupling device. Syringe A will remain attached to the coupling device.

Note: Small air bubbles will remain in the formulation – this is acceptable.

Do not purge the air bubbles from Syringe B as product may be lost!

Step 6

Continue to hold Syringe B upright with the open end at the top. Hold back the white plunger on Syringe B to prevent loss of the product, and attach the safety needle and cap (the safety needle is located under the tray). Gently screw clockwise with approximately a three-quarter turn until the safety needle and cap are secure.

Do not overtighten, as the needle hub may become damaged which could result in leakage of the product during injection. The safety shield may also be damaged if the safety needle and cap are screwed with too much force.

Step 7

Move the safety shield away from the needle and towards the syringe.

Pull off the cap immediately prior to administration.

Note: Should the needle hub appear to be damaged, or leak, the product should NOT be used. The damaged safety needle and cap should NOT be replaced and the product should NOT be injected. In the event of damage to the needle hub, use a new replacement ELIGARD carton.

2.3 Administration Instructions

1. Select an injection site on the abdomen, upper buttocks, or another location with adequate amounts of subcutaneous tissue that does not have excessive pigment, nodules, lesions, or hair and hasn’t recently been used.

2. Cleanse the injection-site area with an alcohol swab (not enclosed).

3. Using the thumb and forefinger, grab and bunch the area of skin around the injection site.

4. Using your dominant hand, insert the needle quickly at a 90° angle to the skin surface. The depth of penetration will depend on the amount and fullness of the subcutaneous tissue and the length of the needle. After the needle is inserted, release the skin.

5. Inject the drug using a slow, steady push and press down on the plunger until the syringe is empty.

Make sure all the drug has been injected before removing the needle.

6. Withdraw the needle quickly at the same 90° angle used for insertion.

7. Immediately following the withdrawal of the needle, activate the safety shield using a finger/thumb or flat surface and push until it completely covers the needle tip and locks into place.

8. An audible and tactile “click” verifies a locked position.

9. Check to confirm the safety shield is fully engaged. Discard all components safely in an appropriate biohazard container.

3 DOSAGE FORMS AND STRENGTHS

ELIGARD is an injectable suspension of leuprolide acetate available in a pre-connected syringe system and packaged with a sterile safety needle and cap (Table 2), a desiccant, prescribing information and instructions for use. The pre-connected syringe system consists of syringe A and syringe B connected using a coupling device. Syringe A contains the in situ polymeric extended release technology and the syringe B contains leuprolide acetate powder. When reconstituted, ELIGARD is administered as a single dose. Refer to Table 10 for details of the description of the dosage form before and after mixing [see How Supplied/Storage and Handling (16)].

Table 2. Specifications for ELIGARD Sterile Safety Needle and Cap

ELIGARD strength | Gauge | Length
7.5 mg | 20-gauge | 5/8-inch
22.5 mg | 20-gauge | 5/8-inch
30 mg | 20-gauge | 5/8-inch
45 mg | 18-gauge | 5/8-inch

4 CONTRAINDICATIONS

Hypersensitivity

ELIGARD is contraindicated in patients with hypersensitivity to GnRH, GnRH agonist analogs or any of the components of ELIGARD. Anaphylactic reactions to synthetic GnRH or GnRH agonist analogs have been reported in the literature.

5 WARNINGS AND PRECAUTIONS

5.1 Tumor Flare

ELIGARD 7.5 mg, 22.5 mg, and 30 mg like other GnRH agonists, causes a transient increase in serum concentrations of testosterone during the first week of treatment. ELIGARD 45 mg causes a transient increase in serum concentrations of testosterone during the first two weeks of treatment. Patients may experience worsening of symptoms or onset of new signs and symptoms during the first few weeks of treatment, including bone pain, neuropathy, hematuria, or bladder outlet obstruction.

Cases of ureteral obstruction and/or spinal cord compression, which may contribute to paralysis with or without fatal complications, have been observed in the treatment of advanced prostate cancer using GnRH agonists.

Patients with metastatic vertebral lesions and/or with urinary tract obstruction should be closely observed during the first few weeks of therapy. If spinal cord compression or ureteral obstruction develops, standard treatment of these complications should be instituted.

5.2 Hyperglycemia and Diabetes

Hyperglycemia and an increased risk of developing diabetes have been reported in men receiving GnRH agonists. Hyperglycemia may represent development of diabetes mellitus or worsening of glycemic control in patients with diabetes. Monitor blood glucose and/or glycosylated hemoglobin (HbA1c) periodically in patients receiving a GnRH agonist and manage with current practice for treatment of hyperglycemia or diabetes.

5.3 Cardiovascular Diseases

Increased risk of developing myocardial infarction, sudden cardiac death and stroke has been reported in association with use of GnRH agonists in men. The risk appears low based on the reported odds ratios, and should be evaluated carefully along with cardiovascular risk factors when determining a treatment for patients with prostate cancer. Patients receiving a GnRH agonist should be monitored for symptoms and signs suggestive of development of cardiovascular disease and be managed according to current clinical practice.

5.4 Effect on QT/QTc Interval

Androgen deprivation therapy may prolong the QT/QTc interval. Providers should consider whether the benefits of androgen deprivation therapy outweigh the potential risks in patients with congenital long QT syndrome, congestive heart failure, frequent electrolyte abnormalities, and in patients taking drugs known to prolong the QT interval. Electrolyte abnormalities should be corrected. Consider periodic monitoring of electrocardiograms and electrolytes.

5.5 Convulsions

Postmarketing reports of convulsions have been observed in patients on leuprolide acetate therapy. These included patients with a history of seizures, epilepsy, cerebrovascular disorders, central nervous system anomalies or tumors, and in patients on concomitant medications that have been associated with convulsions such as bupropion and SSRIs. Convulsions have also been reported in patients in the absence of any of the conditions mentioned above. Patients receiving a GnRH agonist who experience convulsion should be managed according to current clinical practice.

5.6 Severe Cutaneous Adverse Reactions

Severe cutaneous adverse reactions (SCARs), including Steve-Johnson syndrome/toxic epidermal necrolysis (SJS/TEN), and erythema multiforme, occurred in patients receiving ELIGARD [see Adverse Reactions (6.2)].

Monitor patients for the development of SCARs. Advise patients of the signs and symptoms of SCARs (e.g., a prodrome of fever, flu-like symptoms, mucosal lesions, progressive skin rash, or lymphadenopathy).

If a SCAR is suspected, interrupt ELIGARD until the etiology of the reaction has been determined. Consultation with a dermatologist is recommended. If a SCAR is confirmed, or for other grade 4 skin reactions, permanently discontinue ELIGARD.

5.7 Laboratory Tests

Monitor ELIGARD response by periodic measurement of serum concentrations of testosterone and prostate specific antigen.

In the majority of patients, testosterone levels increased above Baseline during the first week, declining thereafter to Baseline levels or below by the end of the second or third week. Castrate levels were generally reached within two to four weeks.

Castrate testosterone levels were maintained for the duration of the treatment with ELIGARD 7.5 mg. No increases to above the castrate level occurred in any of the patients.

Castrate levels were generally maintained for the duration of treatment with ELIGARD 22.5 mg.

Once castrate levels were achieved with ELIGARD 30 mg, most (86/89) patients remained suppressed throughout the study.

Once castrate levels were achieved with ELIGARD 45 mg, one patient (< 1%) experienced a breakthrough, with testosterone levels > 50 ng/dL.

Results of testosterone determinations are dependent on assay methodology. It is advisable to be aware of the type and precision of the assay methodology to make appropriate clinical and therapeutic decisions.

Drug/Laboratory Test Interactions: Therapy with ELIGARD results in suppression of the pituitary-gonadal system. Results of diagnostic tests of pituitary gonadotropic and gonadal functions conducted during and after ELIGARD therapy may be affected.

5.8 Embryo-Fetal Toxicity

Based on findings in animal studies and mechanism of action, ELIGARD may cause fetal harm when administered to a pregnant woman. In animal developmental and reproductive studies, major fetal abnormalities were observed after administration of leuprolide acetate throughout gestation in rats. Advise pregnant patients and females of reproductive potential of the potential risk to the fetus [see Use in Specific Populations (8.1), Clinical Pharmacology (12.1)].

6 ADVERSE REACTIONS

The following clinically significant adverse reactions are described elsewhere in the labeling:

- Tumor Flare [see Warnings and Precautions (5.1)]
- Hyperglycemia and Diabetes [see Warnings and Precautions (5.2)]
- Cardiovascular Disease [see Warnings and Precautions (5.3)]
- Effect on QT/QTc Interval [see Warnings and Precautions (5.4)]
- Convulsions [see Warnings and Precautions (5.5)]
- Severe Cutaneous Adverse Reactions [see Warnings and Precautions (5.6)]

6.1 Clinical Trial Experience

Because clinical trials are conducted under widely varying conditions, adverse reaction rates observed in the clinical trials of a drug cannot be directly compared to rates in the clinical trials of another drug and may not reflect the rates observed in practice.

The safety of all ELIGARD formulations was evaluated in clinical trials involving patients with advanced prostate cancer. In addition, the safety of ELIGARD 7.5 mg was evaluated in 8 surgically castrated males (Table 4). ELIGARD, like other GnRH analogs, caused a transient increase in serum testosterone concentrations during the first one to two weeks of treatment.

Therefore, potential exacerbations of signs and symptoms of the disease during the first weeks of treatment are of concern in patients with vertebral metastases and/or urinary obstruction or hematuria. If these conditions are aggravated, it may lead to neurological problems such as weakness and/or paresthesia of the lower limbs or worsening of urinary symptoms [see Warnings and Precautions (5.7)].

During the clinical trials, injection sites were closely monitored. Refer to Table 3 for a summary of reported injection site adverse reactions.

Table 3. Reported Injection Site Adverse Reactions

ELIGARD | 7.5 mg | 22.5 mg | 30 mg | 45 mg
Study number | AGL9904 | AGL9909 | AGL0001 | AGL0205
Number of patients | 120 | 117 | 90 | 111
Treatment | 1 injection every month up to 6 months | 1 injection every 3 months up to 6 months | 1 injection every 4 months up to 8 months | 1 injection every 6 months up to 12 months
Number of injections | 716 | 230 | 175 | 217
Transient burning/ stinging | 248 (34.6%) injections; 84% reported as mild | 50 (21.7%) injections; 86% reported as mild | 35 (20%) injections; 100% reported as mild3 | 35 (16%) injections; 91.4% reported as mild
Pain (generally brief and mild) | 4.3% of injections (18.3% of patients) | 3.5% of injections (6.0% of patients) | 2.3% of injections2 (3.3% of patients) | 4.6% of injections^4
Erythema (generally brief and mild) | 2.6% of injections (12.5% of patients) | 0.9% of injections^1 (1.7% of patients) | 1.1% of injections (2.2% of patients) | -
Bruising (mild) | 2.5% of injections (11.7% of patients) | 1.7% of injections (3.4% of patients) | - | 2.3% of injections^5
Pruritus | 1.4% of injections (9.2% of patients) | 0.4% of injections (0.9% of patients) | - | -
Induration | 0.4% of injections (2.5% of patients) | - | - | -
Ulceration | 0.1% of injections (> 0.8% of patients) | - | - | -
1. Erythema was reported following 2 injections of ELIGARD 22.5 mg. One report characterized the erythema as mild and it resolved within 7 days. The other report characterized the erythema as moderate and it resolved within 15 days. Neither patient experienced erythema at multiple injection times.
2. A single reaction reported as moderate pain resolved within two minutes and all 3 mild pain reactions resolved within several days following injection of ELIGARD 30 mg.
3. Following injection of ELIGARD 30 mg, three of the 35 burning/stinging reactions were reported as moderate.
4. Transient pain was reported as mild in intensity in nine of ten (90%) events and moderate in intensity in one of ten (10%) events following injection of ELIGARD 45 mg.
5. Mild bruising was reported following 5 (2.3%) study injections and moderate bruising was reported following 2 (<1%) study injections of ELIGARD 45 mg.

These localized adverse reactions were non-recurrent over time. No patient discontinued therapy due to an injection site adverse reaction.

The following possibly or probably related systemic adverse reactions occurred during clinical trials with ELIGARD, and were reported in > 2% of patients (Table 4). Reactions considered not drug-related are excluded.

Table 4. Summary of Possible or Probably Related Systemic Adverse Reactions Reported by > 2% of Patients Treated with ELIGARD

ELIGARD |  |  |  | 7.5 mg | 7.5 mg | 22.5 mg | 30 mg | 45 mg
Study number |  |  |  | AGL9904 | AGL9802 | AGL9909 | AGL0001 | AGL0205
Number of patients |  |  |  | 120 | 8 | 117 | 90 | 111
Treatment |  |  |  | 1 injection every month up to 6 months | 1 injection (surgically castrated patients) | 1 injection every 3 months up to 6 months | 1 injection every 4 months up to 8 months | 1 injection every 6 months up to 12 months
Body system |  |  | Adverse Reaction | Number (percent)
Body as a whole |  |  | Malaise and fatigue | 21 (17.5%) | - | 7 (6.0%) | 12 (13.3%) | 13 (11.7%)
 |  |  | Weakness | - | - | - | - | 4 (3.6%)
Nervous system |  |  | Dizziness | 4 (3.3%) | - | - | 4 (4.4%) | -
Vascular |  |  | Hot flashes/sweats | 68 (56.7%)* | 2 (25.0%)* | 66 (56.4%)* | 66 (73.3%)* | 64 (57.7%)*
Renal/urinary |  |  | Urinary frequency | - | - | 3 (2.6%) | 2 (2.2%) | -
Renal/urinary |  |  | Nocturia | - | - | - | 2 (2.2%) | -
Gastrointestinal |  |  | Nausea | - | - | 4 (3.4%) | 2 (2.2%) | -
Gastrointestinal |  |  | Gastroenteritis/colitis | 3 (2.5%) | - | - | - | -
Skin |  |  | Pruritus | - | - | 3 (2.6%) | - | -
Skin |  |  | Clamminess | - | - | - | 4 (4.4%)* | -
Skin |  |  | Night sweats | - | - | - | 3 (3.3%)* | 3 (2.7%)*
Skin |  |  | Alopecia | - | - | - | 2 (2.2%) | -
Musculoskeletal |  |  | Arthralgia | - | - | 4 (3.4%) | - | -
Musculoskeletal |  |  | Myalgia | - | - | - | 2 (2.2%) | 5 (4.5%)
Musculoskeletal |  |  | Pain in limb | - | - | - | - | 3 (2.7%)
Reproductive |  |  | Testicular atrophy | 6 (5.0%)* | - | - | 4 (4.4%)* | 8 (7.2%)*
Reproductive |  |  | Gynecomastia | - | - | - | 2 (2.2%)* | 4 (3.6%)*
Reproductive |  |  | Testicular pain | - | - | - | 2 (2.2%) | -
Psychiatric |  |  | Decreased libido | - | - | - | 3 (3.3%)* | -
*Expected pharmacological consequences of testosterone suppression.
In the patient populations studied with ELIGARD 7.5 mg, a total of 86 hot flashes/sweats adverse reactions were reported in 70 patients. Of these, 71 reactions (83%) were mild; 14 (16%) were moderate; 1 (1%) was severe.
In the patient population studied with ELIGARD 22.5 mg, a total of 84 hot flashes/sweats adverse reactions were reported in 66 patients. Of these, 73 reactions (87%) were mild; 11 (13%) were moderate; none were severe.
In the patient population studied with ELIGARD 30 mg, a total of 75 hot flash adverse reactions were reported in 66 patients. Of these, 57 reactions (76%) were mild; 16 (21%) were moderate; 2 (3%) were severe.
In the patient population studied with ELIGARD 45 mg, a total of 89 hot flash adverse reactions were reported in 64 patients. Of these, 62 reactions (70%) were mild; 27 (30%) were moderate; none were severe.

In addition, the following possibly or probably related systemic adverse reactions were reported by < 2% of the patients treated with ELIGARD in these clinical studies.

Body system | Adverse Reactions
General | Sweating, insomnia, syncope, rigors, weakness, lethargy
Gastrointestinal | Flatulence, constipation, dyspepsia
Hematologic | Decreased red blood cell count, hematocrit and hemoglobin
Metabolic | Weight gain
Musculoskeletal | Tremor, backache, joint pain, muscle atrophy, limb pain
Nervous | Disturbance of smell and taste, depression, vertigo
Psychiatric | Insomnia, depression, loss of libido*
Renal/urinary | Difficulties with urination, pain on urination, scanty urination, bladder spasm, blood in urine, urinary retention, urinary urgency, incontinence, nocturia, nocturia aggravated
Reproductive/ Urogenital | Testicular soreness/pain, impotence*, decreased libido*, gynecomastia*, breast soreness/tenderness*, testicular atrophy*, erectile dysfunction, penile disorder*, reduced penis size
Skin | Alopecia, clamminess, night sweats*, sweating increased*
Vascular | Hypertension, hypotension
* Expected pharmacological consequences of testosterone suppression.

Changes in Bone Density: Decreased bone density has been reported in the medical literature in men who have had orchiectomy or who have been treated with a GnRH agonist analog. It can be anticipated that long periods of medical castration in men will have effects on bone density.

6.2 Postmarketing Experience

The following adverse reactions have been identified during post-approval use of ELIGARD. Because these reactions are reported voluntarily from a population of uncertain size, it is not always possible to reliably estimate their frequency or establish a causal relationship to drug exposure.

Pituitary apoplexy- During postmarketing surveillance, rare cases of pituitary apoplexy (a clinical syndrome secondary to infarction of the pituitary gland) have been reported after the administration of gonadotropin-releasing hormone agonists. In a majority of these cases, a pituitary adenoma was diagnosed with a majority of pituitary apoplexy cases occurring within 2 weeks of the first dose, and some within the first hour. In these cases, pituitary apoplexy has presented as sudden headache, vomiting, visual changes, ophthalmoplegia, altered mental status, and sometimes cardiovascular collapse. Immediate medical attention has been required.

Nervous System- Convulsions

Respiratory System- Interstitial lung disease

Skin reactions- Erythema multiforme, SJS/TEN

8 USE IN SPECIFIC POPULATIONS

8.1 Pregnancy

Risk Summary
Based on findings in animal studies and mechanism of action, ELIGARD may cause fetal harm when administered to a pregnant woman [see Clinical Pharmacology (12.1)]. There are no available data in pregnant women to inform the drug-associated risk. Expected hormonal changes that occur with ELIGARD treatment increase the risk for pregnancy loss. In animal developmental and reproductive studies, major fetal abnormalities were observed after administration of leuprolide acetate throughout gestation in rats. Advise pregnant patients and females of reproductive potential of the potential risk to the fetus (see Data).

Data

Animal Data
In animal developmental and reproductive studies, major fetal abnormalities were observed after administration of leuprolide acetate throughout gestation. There were increased fetal mortality and decreased fetal weights in rats and rabbits. The effects of fetal mortality are expected consequences of the alterations in hormonal levels brought about by this drug.

8.2 Lactation

The safety and efficacy of ELIGARD have not been established in females. There is no information regarding the presence of ELIGARD in human milk, the effects on the breastfed child, or the effects on milk production. Because many drugs are excreted in human milk and because of the potential for serious adverse reactions in a breastfed child from ELIGARD, a decision should be made to discontinue breastfeeding or discontinue the drug, taking into account the importance of the drug to the mother.

8.3 Females and Males of Reproductive Potential

Infertility
Males
Based on mechanism of action, ELIGARD may impair fertility in males of reproductive potential [see Clinical Pharmacology (12.1)].

8.4 Pediatric Use

The safety and effectiveness of ELIGARD in pediatric patients have not been established.

8.5 Geriatric Use

The majority of the patients (approximately 70%) studied in the clinical trials were age 70 and older. Clinical studies of ELIGARD did not include sufficient numbers of younger adult patients to determine if patients 65 years of age and older respond differently than younger adult patients.

11 DESCRIPTION

ELIGARD is a sterile polymeric matrix formulation of leuprolide acetate, a GnRH agonist, for subcutaneous injection. It is designed to deliver leuprolide acetate at a controlled rate over a one-, three-, four, or six-month therapeutic period.

Leuprolide acetate is a synthetic nonapeptide analog of naturally occurring gonadotropin releasing hormone (GnRH) that, when given continuously, inhibits pituitary gonadotropin secretion and suppresses testicular and ovarian steroidogenesis. The analog possesses greater potency than the natural hormone. The chemical name is 5-oxo-L-prolyl-L-histidyl-L-tryptophyl-L-seryl-L-tyrosyl-D-leucyl-L-leucyl-L-arginyl-N-ethyl-L-prolinamide acetate (salt) with the following structural formula:

ELIGARD is supplied as a pre-connected syringe system comprised of two prefilled syringes (syringe A and syringe B) connected using a coupling device. Immediately prior to administration, the contents of the pre-connected syringe system are mixed until homogenous. ELIGARD is administered subcutaneously, where it forms a solid drug delivery depot.

Syringe A contains the in situ polymeric extended release technology consisting of a biodegradable poly (DL-lactide-co-glycolide) (PLGH or PLG) polymer formulation dissolved in a biocompatible solvent, N-methyl-2-pyrrolidone (NMP) and syringe B contains leuprolide acetate.

Refer to Table 5 for the delivery system composition and reconstituted product formulation for each ELIGARD product.

Table 5. ELIGARD Delivery System Composition and Reconstituted Product Formulation

ELIGARD |  | 7.5 mg | 22.5 mg | 30 mg | 45 mg
In situ polymeric extended release technology | Polymer | PLGH | PLG | PLG | PLG
In situ polymeric extended release technology | Polymer description | Copolymer containing carboxyl endgroups | Copolymer with hexanediol | Copolymer with hexanediol | Copolymer with hexanediol
In situ polymeric extended release technology | Polymer DL-lactide to glycolide molar ratio | 50:50 | 75:25 | 75:25 | 85:15
Reconstituted product | Polymer delivered | 82.5 mg | 158.6 mg | 211.5 mg | 165 mg
Reconstituted product | NMP delivered | 160.0 mg | 193.9 mg | 258.5 mg | 165 mg
Reconstituted product | Leuprolide acetate delivered | 7.5 mg | 22.5 mg | 30 mg | 45 mg
Reconstituted product | Approximate Leuprolide free base equivalent | 7.0 mg | 21 mg | 28 mg | 42 mg
Reconstituted product | Approximate administered formulation weight | 250 mg | 375 mg | 500 mg | 375 mg
Reconstituted product | Approximate injection volume | 0.25 mL | 0.375 mL | 0.5 mL | 0.375 mL

12 CLINICAL PHARMACOLOGY

12.1 Mechanism of Action

Leuprolide acetate, a gonadotropin releasing hormone (GnRH) agonist, acts as an inhibitor of gonadotropin secretion when given continuously in therapeutic doses. Animal and human studies indicate that after an initial stimulation, chronic administration of leuprolide acetate results in suppression of testicular and ovarian steroidogenesis. This effect is reversible upon discontinuation of drug therapy.

12.2 Pharmacodynamics

Following initial administration, ELIGARD causes an initial increase in serum luteinizing hormone (LH) and follicle stimulating hormone (FSH) levels with subsequent increases in serum levels of testosterone. Administration of ELIGARD leads to sustained suppression of pituitary gonadotropins, and serum levels of testosterone consequently fall into the range normally seen in surgically castrated men approximately 21 days after initiation of therapy. Continuation of therapy with leuprolide acetate in patients with prostate cancer maintained testosterone below the castrate level for up to five years.

Following the first dose of ELIGARD, mean serum testosterone concentrations transiently increased, then fell to below castrate threshold (< 50 ng/dL) within three weeks, and generally remained below castrate threshold levels throughout treatment for all ELIGARD concentrations. Mean serum testosterone concentrations fell to < 20 ng/dL within five weeks for all ELIGARD concentrations.

12.3 Pharmacokinetics

Absorption
ELIGARD 7.5 mg
Following a single injection of ELIGARD 7.5 mg for 1-month administration in patients, the mean peak plasma concentration was 25.3 ng/mL (Cmax) at 5 hours;at the end of the 4 week dosing interval the mean concentration declined to 0.42 ng/mL.

ELIGARD 22.5 mg
Following a single injection of ELIGARD 22.5 mg for 3-month administration in patients, the mean peak plasma concentration was 127 ng/mL (Cmax) at 5 hours; at the end of the 12 week dosing interval the mean concentration declined to 0.34 ng/mL.

ELIGARD 30 mg
Following a single injection of ELIGARD 30 mg for 4-month administration in patients, the mean peak plasma concentration was 150 ng/mL (Cmax) at 3.3 hours; at the end of the 16 week dosing interval the mean concentration declined to 0.1 ng/mL.

ELIGARD 45 mg
Following a single injection of ELIGARD 45 mg for 6-month administration in patients, the mean peak plasma concentration was 82 ng/mL at 4.5 hours (Cmax); at the end of the 24 week dosing interval the mean concentration declined to 0.2 ng/mL.

There was no evidence of significant accumulation during repeated dosing.

Distribution
The mean steady-state volume of distribution of leuprolide following intravenous bolus administration to healthy male volunteers was 27 L. In vitro binding to human plasma proteins ranged from 43% to 49%.

Elimination
After the initial increase following each subcutaneous injection, serum concentration range was 0.1 – 2.00 ng/mL.

In healthy male volunteers, a 1-mg bolus of leuprolide administered intravenously revealed that the mean systemic clearance was 8.34 L/h, with a terminal elimination half-life of approximately 3 hours based on a two compartment model.

Metabolism
No drug metabolism study was conducted with ELIGARD. Upon administration with different leuprolide acetate formulations, the major metabolite of leuprolide acetate is a pentapeptide (M-1) metabolite.

Excretion
No drug excretion study was conducted with ELIGARD.

Specific Populations
Geriatrics [see Use in Specific Populations (8.5)]

Race
In patients studied, mean serum leuprolide concentrations were similar regardless of race. Refer to Table 6 for distribution of study patients by race.

Table 6. Race Characterization of ELIGARD Study Patients (n)

Race | ELIGARD 7.5 mg | ELIGARD 22.5 mg | ELIGARD 30 mg | ELIGARD 45 mg
White | 26 | 19 | 18 | 17
Black | - | 4 | 4 | 7
Hispanic | 2 | 2 | 2 | 3

Renal and Hepatic Insufficiency
The pharmacokinetics of ELIGARD in hepatically and renally impaired patients have not been determined.

13 NONCLINICAL TOXICOLOGY

13.1 Carcinogenesis, Mutagenesis, Impairment of Fertility

Two-year carcinogenicity studies were conducted with leuprolide acetate in rats and mice. In rats, a dose-related increase of benign pituitary hyperplasia and benign pituitary adenomas was noted at 24 months when the drug was administered subcutaneously at high daily doses (0.6 to 4 mg/kg). There was a significant but not dose-related increase of pancreatic islet-cell adenomas in females and of testicular interstitial cell adenomas in males (highest incidence in the low dose group). In mice, no leuprolide acetate-induced tumors or pituitary abnormalities were observed at a dose as high as 60 mg/kg for two years. Patients have been treated with leuprolide acetate for up to three years with doses as high as 10 mg/day and for two years with doses as high as 20 mg/day without demonstrable pituitary abnormalities. No carcinogenicity studies have been conducted with ELIGARD.

Mutagenicity studies have been performed with leuprolide acetate using bacterial and mammalian systems and with ELIGARD 7.5 mg in bacterial systems. These studies provided no evidence of a mutagenic potential.

14 CLINICAL STUDIES

One open-label, multicenter study was conducted with each ELIGARD formulation (7.5 mg, 22.5 mg, 30 mg, and 45 mg) in patients with Jewett stage A though D prostate cancer who were treated with at least a single injection of study drug (Table 7). The efficacy outcome measure was medical castration rate, defined as achieving and maintaining serum testosterone suppression to ≤ 50 ng/dL (Figures 1-4).

During the AGL9904 study using ELIGARD 7.5 mg, once testosterone suppression below 50 ng/dL was achieved, no patients (0%) demonstrated breakthrough (concentration > 50 ng/dL) at any time in the study.

During the AGL9909 study using ELIGARD 22.5 mg, once testosterone suppression below 50 ng/dL was achieved, one patient (< 1%) demonstrated breakthrough following the initial injection; that patient remained below 50 ng/dL following the second injection.

During the AGL0001 study using ELIGARD 30 mg, once testosterone suppression below 50 ng/dL was achieved, three patients (3%) demonstrated breakthrough. In the first of these patients, a single serum testosterone concentration of 53 ng/dL was reported on the day after the second injection. In this patient, suppression below 50 ng/dL was reported for all other time points. In the second patient, a serum testosterone concentration of 66 ng/dL was reported immediately prior to the second injection. This rose to a maximum concentration of 147 ng/dL on the second day after the second injection. In this patient, suppression below 50 ng/dL was again reached on the seventh day after the second injection and was maintained thereafter. In the final patient, serum testosterone concentrations > 50 ng/dL were reported at 2 and at 8 hours after the second injection. Serum testosterone concentration rose to a maximum of 110 ng/dL on the third day after the second injection. In this patient, suppression below 50 ng/dL was again reached eighteen days after the second injection and was maintained until the final day of the study, when a single serum testosterone concentration of 55 ng/dL was reported.

During the AGL0205 study using ELIGARD 45 mg, once testosterone suppression below 50 ng/dL was achieved, one patient (<1%) demonstrated breakthrough. This patient reached castrate suppression below 50 ng/dL at Day 21 and remained suppressed until Day 308 when his testosterone level rose to 112 ng/dL. At Month 12 (Day 336), his testosterone was 210 ng/dL.

Table 7. Summary of Patients in ELIGARD Clinical Studies

ELIGARD |  |  | 7.5 mg | 22.5 mg | 30 mg | 45 mg
Study number |  |  | AGL9904 | AGL9909 | AGL0001 | AGL0205
Total number of patients |  |  | 120 (117 completed) | 117^2 (111 completed^3) | 90 (82 completed^4) | 111 (103 completed^5)
Jewett stages | Stage A |  | ‑ | 2 | 2 | 5
Jewett stages | Stage B |  | ‑ | 19 | 38 | 43
Jewett stages | Stage C |  | 89 | 60 | 16 | 19
Jewett stages | Stage D |  | 31 | 36 | 34 | 44
Treatment |  |  | 6 monthly injections | 1 injection (4 patients) | 1 injection (5 patients) | 1 injection (5 patients)
Treatment |  |  | 6 monthly injections | 2 injections, one every three months (113 patients) | 2 injections, one every four months (85 patients) | 2 injections, one every six months (106 patients)
Duration of therapy |  |  | 6 months | 6 months | 8 months | 12 months
Mean testosterone concentration (ng/dL) |  | Baseline | 361.3 | 367.1 | 385.5 | 367.7
Mean testosterone concentration (ng/dL) |  | Day 2 | 574.6 (Day 3) | 588.0 | 610.0 | 588.6
Mean testosterone concentration (ng/dL) |  | Day 14 | Below Baseline (Day 10) | Below Baseline | Below Baseline | Below Baseline
Mean testosterone concentration (ng/dL) |  | Day 28 | 21.8 | 27.7 (Day 21) | 17.2 | 16.7
Mean testosterone concentration (ng/dL) |  | Conclusion | 6.1 | 10.1 | 12.4 | 12.6
Number of patients with testosterone ≤ 50 ng/dL |  | Day 28 | 112 of 119 (94.1%) | 115 of 116 (99%) | 85 of 89 (96%) | 108 of 109 (99.1%)
Number of patients with testosterone ≤ 50 ng/dL |  | Day 35 | ‑ | 116 (100%) | ‑ | -
Number of patients with testosterone ≤ 50 ng/dL |  | Day 42 | 118 (100%) | ‑ | 89 (100%) | -
Number of patients with testosterone ≤ 50 ng/dL |  | Conclusion | 117^1 (100%) | 111 (100%) | 81 (99%) | 102 (99%)
Number of patients with testosterone ≤ 20 ng/dL |  | Day 28 | 90 of 119 (76%) | 94 of 116 (81%) | 60 of 89 (67%) | 87 of 109 (80%)
1. Two patients withdrew for reasons unrelated to drug.
2. One patient received less than a full dose at Baseline, never attained castration, and was withdrawn at Day 73 and given an alternate treatment.
3. All non-evaluable patients who attained castration by Day 28 maintained castration at each time point up to and including the time of withdrawal.
4. One patient withdrew on Day 14. All 7 non-evaluable patients who had achieved castration by Day 28 maintained castration at each time point, up to and including the time of withdrawal.
5. Two patients were withdrawn prior to the Month 1 blood draw. One patient did not achieve castration and was withdrawn on Day 85. All 5 non-evaluable patients who attained castration by Day 28, maintained castration at each time point up to and including the time of withdrawal.

Figure 1. ELIGARD 7.5 mg Mean Serum Testosterone Concentrations (n=117)

Figure 2. ELIGARD 22.5 mg Mean Serum Testosterone Concentrations (n=111)

Figure 3. ELIGARD 30 mg Mean Serum Testosterone Concentrations (n=90)

Figure 4. ELIGARD 45 mg Mean Serum Testosterone Concentrations (n=103)

Serum PSA decreased in all patients in all studies whose Baseline values were elevated above the normal limit. Refer to Table 8 for a summary of the effectiveness of ELIGARD in reducing serum PSA values.

Table 8. Effect of ELIGARD on Patient Serum PSA Values

ELIGARD | 7.5 mg | 22.5 mg | 30 mg | 45 mg
Mean PSA reduction at study conclusion | 94% | 98% | 86% | 97%
Patients with normal PSA at study conclusion* | 94% | 91% | 93% | 95%
*Among patients who presented with elevated levels at Baseline

Other secondary efficacy endpoints evaluated included WHO performance status, bone pain, urinary pain and urinary signs and symptoms. Refer to Table 9 for a summary of these endpoints.

Table 9. Secondary Efficacy Endpoints

ELIGARD |  | 7.5 mg | 22.5 mg | 30 mg | 45 mg
Baseline | WHO Status = 0^1 | 88% | 94% | 90% | 90%
Baseline | WHO Status = 1^2 | 11% | 6% | 10% | 7%
Baseline | WHO Status = 2^3 | - | - | - | 3%
Baseline | Mean bone pain^4 (range) | 1.22 (1-9) | 1.20 (1-9) | 1.20 (1-7) | 1.38 (1-7)
Baseline | Mean urinary pain (range) | 1.12 (1-5) | 1.02 (1-2) | 1.01 (1-2) | 1.22 (1-8)
 | Mean urinary signs and symptoms (range) | Low | 1.09 (1-4) | Low | Low
 | Number of patients with prostate abnormalities | 102 (85%) | 96 (82%) | 66 (73%) | 89 (80%)
 |  | Month 6 | Month 6 | Month 8 | Month 12
Follow-up | WHO status = 0 | Unchanged | 96% | 87% | 94%
Follow-up | WHO status = 1 | Unchanged | 4% | 12% | 5%
 | WHO status = 2 | - | - | 1% | 1%
 | Mean bone pain (range) | 1.26 (1-7) | 1.22 (1-5) | 1.19 (1-8) | 1.31 (1-8)
 | Mean urinary pain (range) | 1.07 (1-8) | 1.10 (1-8) | 1.00 (1-1) | 1.07 (1-5)
 | Mean urinary signs and symptoms (range) | Modestly decreased | 1.18 (1-7) | Modestly decreased | Modestly decreased
 | Number of patients with prostate abnormalities | 77 (64%) | 76 (65%) | 54 (60%) | 60 (58%)
1. WHO status = 0 classified as “fully active.” 2. WHO status = 1 classified as “restricted in strenuous activity but ambulatory and able to carry out work of a light or sedentary nature.” 3. WHO status = 2 classified as “ambulatory but unable to carry out work activities.” 4. Pain score scale: 1 (no pain) to 10 (worst pain possible).

16 HOW SUPPLIED/STORAGE AND HANDLING

How Supplied

ELIGARD is supplied as a single-dose, two syringe-mixing system with a sterile safety needle and cap. ELIGARD is available as follows (Table 10):

Table 10. ELIGARD Product Presentations

ELIGARD strength | NDC number | Description of Syringe A with the delivery system | Description of Syringe B with leuprolide acetate | Description of the suspension after mixing
7.5 mg | 62935-756-80 | Light tan to tan, clear, viscous solution | White to off white powder | Light tan to tan
22.5 mg | 62935-227-10 | Colorless to pale yellow, clear viscous solution | White to off white powder | Colorless to pale yellow
30 mg | 62935-306-40 | Colorless to pale yellow, clear viscous solution | White to off white powder | Colorless to pale yellow
45 mg | 62935-461-50 | Colorless to pale yellow, clear viscous solution | White to off white powder | Colorless to pale yellow

Storage

Store at 2°C to 8°C (36°F to 46°F)

Once outside the refrigerator this product may be stored in its original packaging at room temperature 15°C to 30°C (59°F to 86°F) for up to eight weeks prior to mixing and administration.

17 PATIENT COUNSELING INFORMATION

Hypersensitivity

- Inform patients that if they have experienced hypersensitivity with other GnRH agonist drugs like ELIGARD, ELIGARD is contraindicated [see Contraindications (4)].

Tumor Flare

- Inform patients that ELIGARD can cause tumor flare during the first weeks of treatment. Inform patients that the increase in testosterone can cause an increase in urinary symptoms or pain. Advise patients to contact their healthcare provider if ureteral obstruction, spinal cord compression, paralysis, or new or worsened symptoms occur after beginning ELIGARD treatment [see Warnings and Precautions (5.1)].

Hyperglycemia and Diabetes

- Advise patients that there is an increased risk of hyperglycemia and diabetes with ELIGARD therapy. Inform patients that periodic monitoring for hyperglycemia and diabetes is required when being treated with ELIGARD [see Warnings and Precautions (5.2)].

Cardiovascular Disease

- Inform patients that there is an increased risk of myocardial infarction, sudden cardiac death, and stroke with ELIGARD treatment. Advise patients to immediately report signs and symptoms associated with these events to their healthcare provider for evaluation [see Warnings and Precautions (5.3)].

Severe Cutaneous Adverse Reactions

- Inform patients that severe cutaneous adverse reactions (SCARs), including Stevens-Johnson syndrome (SJS) and toxic epidermal necrolysis (TEN), which may be life threatening or fatal, may occur during treatment with ELIGARD. Advise patients to contact their healthcare provider or seek medical attention right away if they experience signs or symptoms of SCARs [see Warnings and Precautions (5.6)].

Injection Site Reactions

- Inform patients that injection site related adverse reactions may occur such as transient burning/stinging, pain, bruising, and redness. Advise patients to contact their healthcare provider if they experience rash or severe injection site reactions [see Adverse Reactions (6.1)].

Urogenital Disorders

- Advise patients that ELIGARD may cause impotence.

Infertility

- Inform patients that ELIGARD may cause infertility [see Use In Specific Populations (8.3)].

Continuation of ELIGARD Treatment:

- Inform patients that ELIGARD is usually continued, often with additional medication, after the development of non-metastatic and metastatic castration-resistant prostate cancer [see Dosage and Administration (2.1)].

Manufactured by: Tolmar, Fort Collins, CO 80526

©2025 Tolmar

04006512 Rev. 5 02/2025

INSTRUCTIONS FOR USE

Follow the detailed instructions below to ensure correct preparation of ELIGARD prior to administration:

Step 1

Use aseptic technique throughout the procedure. Gloves are recommended during mixing and administration.

Allow the product to reach room temperature before mixing. Once mixed, the product must be administered within 30 minutes or it should be discarded.

On a clean field open the tray by tearing off the foil from the corner and remove the contents. Discard the desiccant pack. Remove the pre-connected syringe system from the tray. Open the sterile safety needle package by peeling back the paper tab. Note: Syringe A and Syringe B should not be lined-up yet. The product should only be administered with the co-packaged, sterile safety needle.

Step 2

Grasp the latching button on the coupling device with your finger and thumb and press until you hear a snapping sound. The two syringes will be aligned.

Do not bend the pre-connected syringe system.

Step 3

Holding the syringes in a horizontal position, transfer the liquid contents of Syringe A into the leuprolide acetate powder contained in Syringe B. Thoroughly mix the product for 60 cycles by pushing the contents back and forth between both syringes to obtain a uniform suspension.

- A cycle is one push of the Syringe A plunger and one push of the Syringe B plunger.
- When thoroughly mixed, the suspension will appear light tan to tan (ELIGARD 7.5 mg) or colorless to pale yellow (ELIGARD 22.5 mg, 30 mg, and 45 mg).

Note: Product must be mixed as described; shaking will NOT provide adequate mixing. Do not bend.

Step 4

After mixing, hold the syringes vertically (upright) with Syringe B (wide syringe) on the bottom. The syringes should remain securely coupled. Transfer all of the mixed product into Syringe B by depressing the Syringe A plunger and slightly withdrawing the Syringe B plunger.

Step 5

While ensuring the Syringe A plunger is fully pushed down, hold the coupling device and unscrew Syringe B. This will disconnect Syringe B from the coupling device. Syringe A will remain attached to the coupling device.

Note: Small air bubbles will remain in the formulation – this is acceptable.

Do not purge the air bubbles from Syringe B as product may be lost!

Step 6

Continue to hold Syringe B upright with the open end at the top. Hold back the white plunger on Syringe B to prevent loss of the product, and attach the safety needle and cap (the safety needle is located under the tray). Gently screw clockwise with approximately a three-quarter turn until the safety needle and cap are secure.

Do not overtighten, as the needle hub may become damaged which could result in leakage of the product during injection. The safety shield may also be damaged if the safety needle and cap are screwed with too much force.

Step 7

Move the safety shield away from the needle and towards the syringe.

Pull off the cap immediately prior to administration.

Note: Should the needle hub appear to be damaged, or leak, the product should NOT be used. The damaged safety needle and cap should NOT be replaced and the product should NOT be injected. In the event of damage to the needle hub, use a new replacement ELIGARD carton.

Follow the detailed instructions below to ensure correct administration of ELIGARD:

1. Select an injection site on the abdomen, upper buttocks, or another location with adequate amounts of subcutaneous tissue that does not have excessive pigment, nodules, lesions, or hair and hasn’t recently been used.

2. Cleanse the injection-site area with an alcohol swab (not enclosed).

3. Using the thumb and forefinger, grab and bunch the area of skin around the injection site.

4. Using your dominant hand, insert the needle quickly at a 90° angle to the skin surface. The depth of penetration will depend on the amount and fullness of the subcutaneous tissue and the length of the needle. After the needle is inserted, release the skin.

5. Inject the drug using a slow, steady push and press down on the plunger until the syringe is empty.

Make sure all the drug has been injected before removing the needle.

6. Withdraw the needle quickly at the same 90° angle used for insertion.

7. Immediately following the withdrawal of the needle, activate the safety shield using a finger/thumb or flat surface and push until it completely covers the needle tip and locks into place.

8. An audible and tactile “click” verifies a locked position.

9. Check to confirm the safety shield is fully engaged. Discard all components safely in an appropriate biohazard container.

©2025 Tolmar

Manufactured by: Tolmar, Fort Collins, CO 80526 04006512 Rev. 5 02/2025